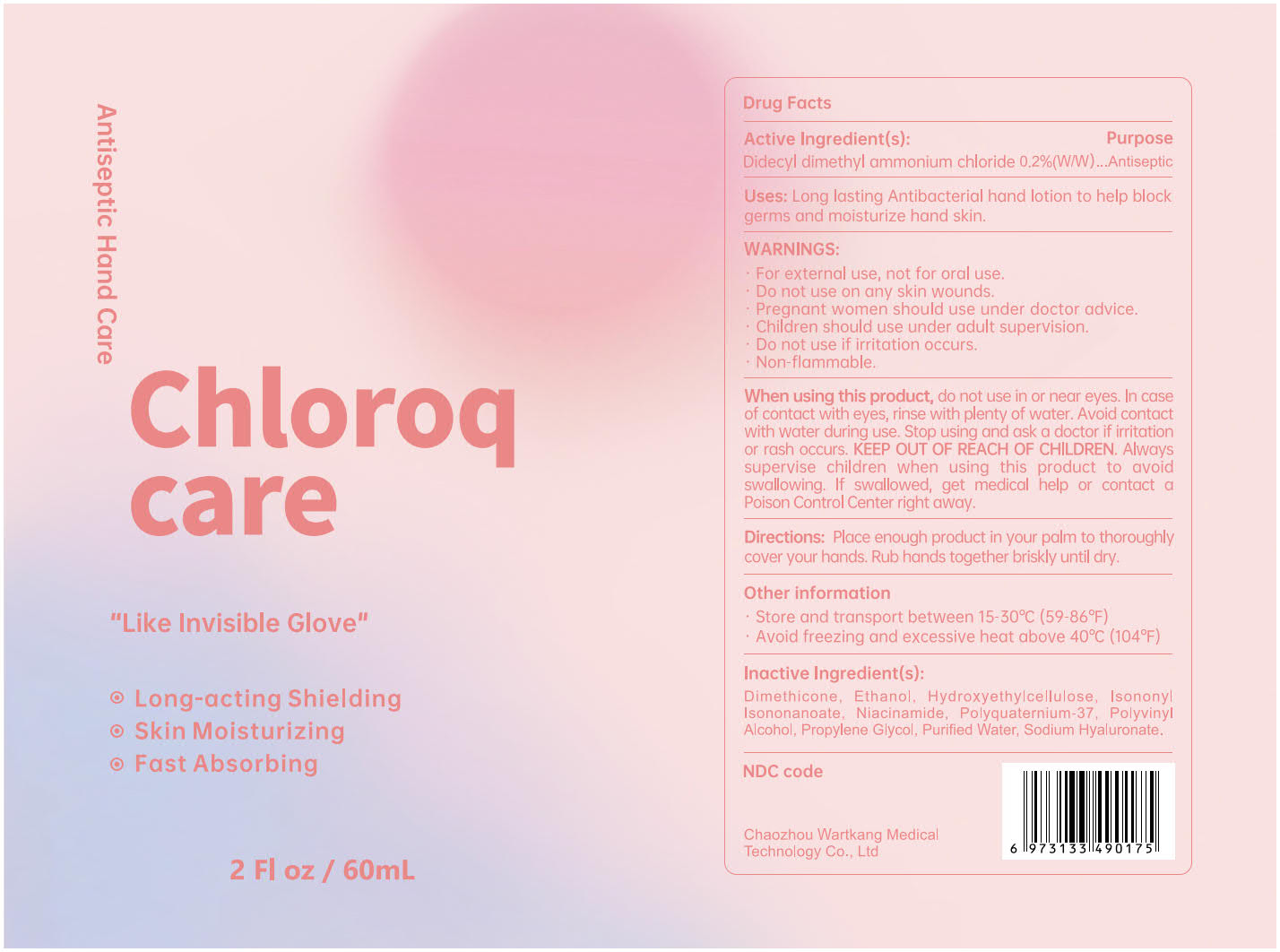 DRUG LABEL: Chloroqcare Antiseptic Hand Care
NDC: 82370-101 | Form: LIQUID
Manufacturer: Wartkang Medical Technology Co., Ltd
Category: otc | Type: HUMAN OTC DRUG LABEL
Date: 20211109

ACTIVE INGREDIENTS: DIDECYLDIMONIUM CHLORIDE 117 mg/60 mL
INACTIVE INGREDIENTS: HYDROXYETHYL CELLULOSE, UNSPECIFIED; ISONONYL ISONONANOATE; PROPYLENE GLYCOL; HYALURONATE SODIUM; ALCOHOL; DIMETHICONE; WATER; NIACINAMIDE; POLYVINYL ALCOHOL, UNSPECIFIED; POLYQUATERNIUM-37 (25000 MPA.S)

Chloroqcare Antiseptic Hand Care, 60mL, Didecyldimonium Chloride 0.2%

Active Ingredient(s)

Didecyldimonium Chloride 0.2% w/w. Purpose: Antiseptic

Purpose

Antiseptic, Hand Sanitizer

Uses

Long lasting Antibacterial hand sanitizer to help back germs and moisturize hand skin.

Warnings

- For external use, not for oral use.
- Do not use on any skin wounds.
- Pregnant women should use under doctor advice.
- Children should use under adult supervision.
- Do not use if irritation occurs.
- Non-flammable.

Do not use on any skin wounds. Do not use if irritation occurs.

When using this product, do not use in or near eyes. In case of contact with eyes, rinse with plenty of water. Avoid contact with water during use. Stop using and ask a doctor if irritation or rash occurs. KEEP OUT OF REACH OF CHILDREN. Always supervise children when using this product to avoid swallowing. If swallowed, get medical help or contact a Poison Control Center right away.

STOP USE

Stop using and ask a doctor if irritation or rash occurs.

KEEP OUT OF REACH OF CHILDREN. Always supervise children when using this product to avoid swallowing. If swallowed, get medical help or contact a Poison Control Center right away.

Directions

Place enough product in your palm to thoroughly cover your hands. Rub hands together briskly until dry.

Other information

- Store and transport between 15-30℃ (59-86℉)
- Avoid freezing and excessive heat above 40℃ (104℉)

Inactive Ingredient(s)

Dimethicone, Ethanol, Hydroxyethylcellulose, Isononyl Isononanoate, Niacinamide, Polyquaternium-37, Polyvinyl Alcohol, Propylene Glycol, Purified Water, Sodium Hyaluronate

Package Label - Principal Display Panel

Chloroqcare Antiseptic Hand Care, 60mL, Didecyldimonium Chloride 0.2%